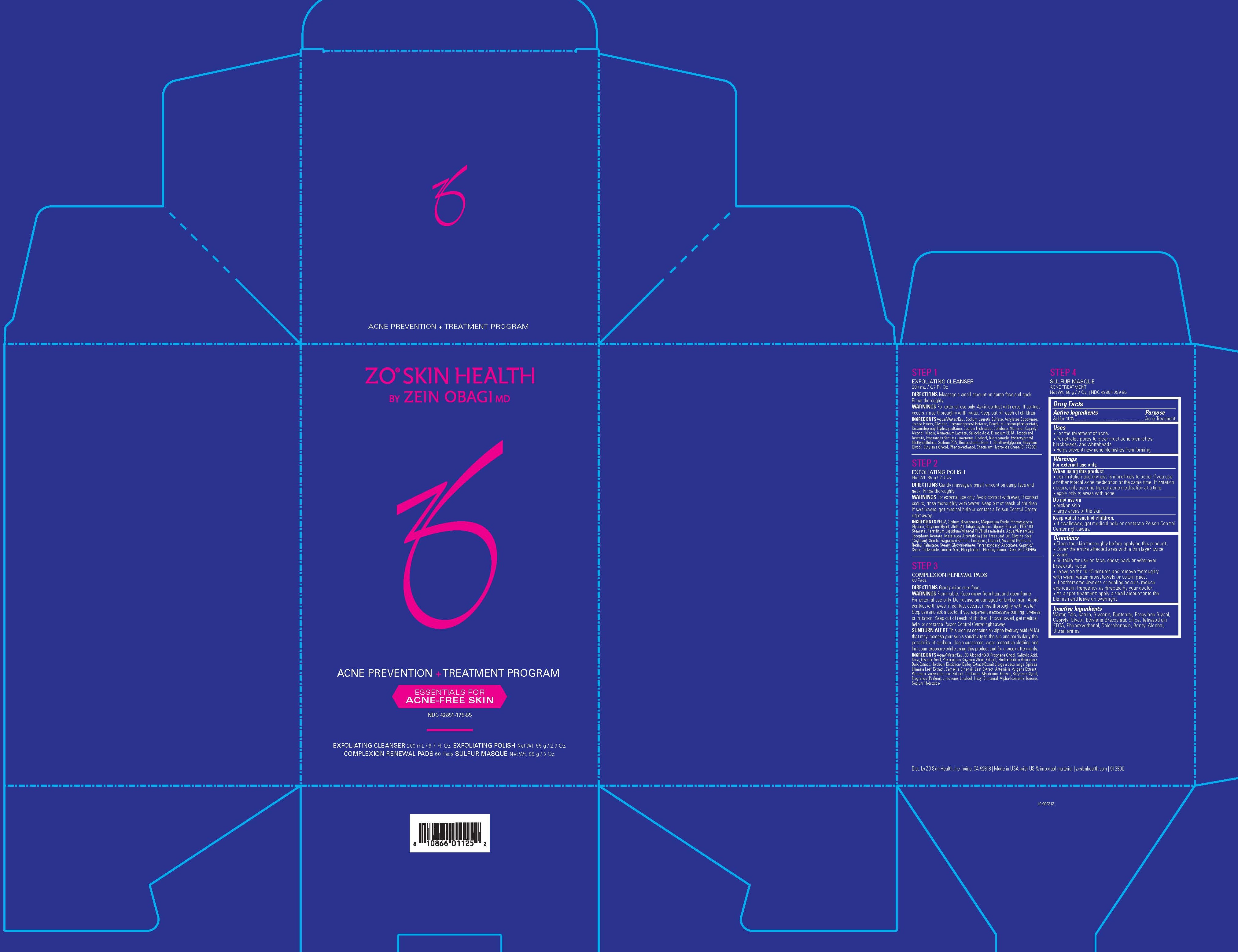 DRUG LABEL: ZO Skin Health Acne Prevention Plus Treatment Program
NDC: 42851-175 | Form: KIT | Route: TOPICAL
Manufacturer: ZO Skin Health, Inc.
Category: otc | Type: HUMAN OTC DRUG LABEL
Date: 20200424

ACTIVE INGREDIENTS: SULFUR 100 mg/1 g
INACTIVE INGREDIENTS: WATER; TALC; KAOLIN; GLYCERIN; BENTONITE; PROPYLENE GLYCOL; PHENOXYETHANOL; ETHYLENE BRASSYLATE; CHLORPHENESIN; BENZYL ALCOHOL; CAPRYLYL GLYCOL; SILICON DIOXIDE; EDETATE SODIUM; ULTRAMARINE BLUE

ZO® Skin Health Acne Prevention + Treatment Program (NDC 42851-175-85)
Exfoliating Cleanser 200 mL
Exfoliating Polish 65 g
Complexion Renewal Pads 60 ct
Sulfur Masque (85 g) NDC 42851-089-85 NPN 80061274

SULFUR MASQUE Acne Treatment

Drug Facts

Active ingredients

Sulfur 10%

Purpose

Acne Treatment

Uses

For the treatment of acne. Penetrates pores to clear most acne blemishes, blackheads and whiteheads. Helps prevent new acne blemishes from forming.

Warnings

For external use only.

When using this product

- Skin irritation and dryness is more likely to occur if you use another topical acne medication at the same time. If irritation occurs, only use one topical acne medication at a time.
- Apply only to areas with acne.

Do Not Use On

- Broken skin
- Large areas of skin.

Keep out of reach of children. If swallowed, get medical help or contact a Poison Control Center right away.

Directions

- Clean the skin thoroughly before applying this product.
- Cover the entire affected area with a thin layer twice a week.
- Leave on for 10-15 minutes and remove thoroughly with warm water, moist towels or cotton pads.
- if bothersome dryness or peeling occurs, reduce application frequency as directed by your doctor.
- As a spot treatment: apply a small amount onto the blemish and leave on overnight.

Inactive ingredients

Water, Talc, Kaolin, Glycerin, Bentonite, Propylene Glycol, Caprylyl Glycol, Ethylene Brassylate, Silica, Tetrasodium EDTA, Phenoxyethanol, Chlorphenesin, Benzyl Alcohol, Ultramarines.

Dist. by ZO Skin Health, Inc. Irvine, CA 92618

Made in USA with US & imported material

PRINCIPAL DISPLAY PANEL - Kit Carton

ZO® SKIN HEALTH
BY ZEIN OBAGI MD

ACNE PREVENTION
+ TREATMENT PROGRAM

ESSENTIALS FOR
ACNE-FREE SKIN

NDC 42851-175-85